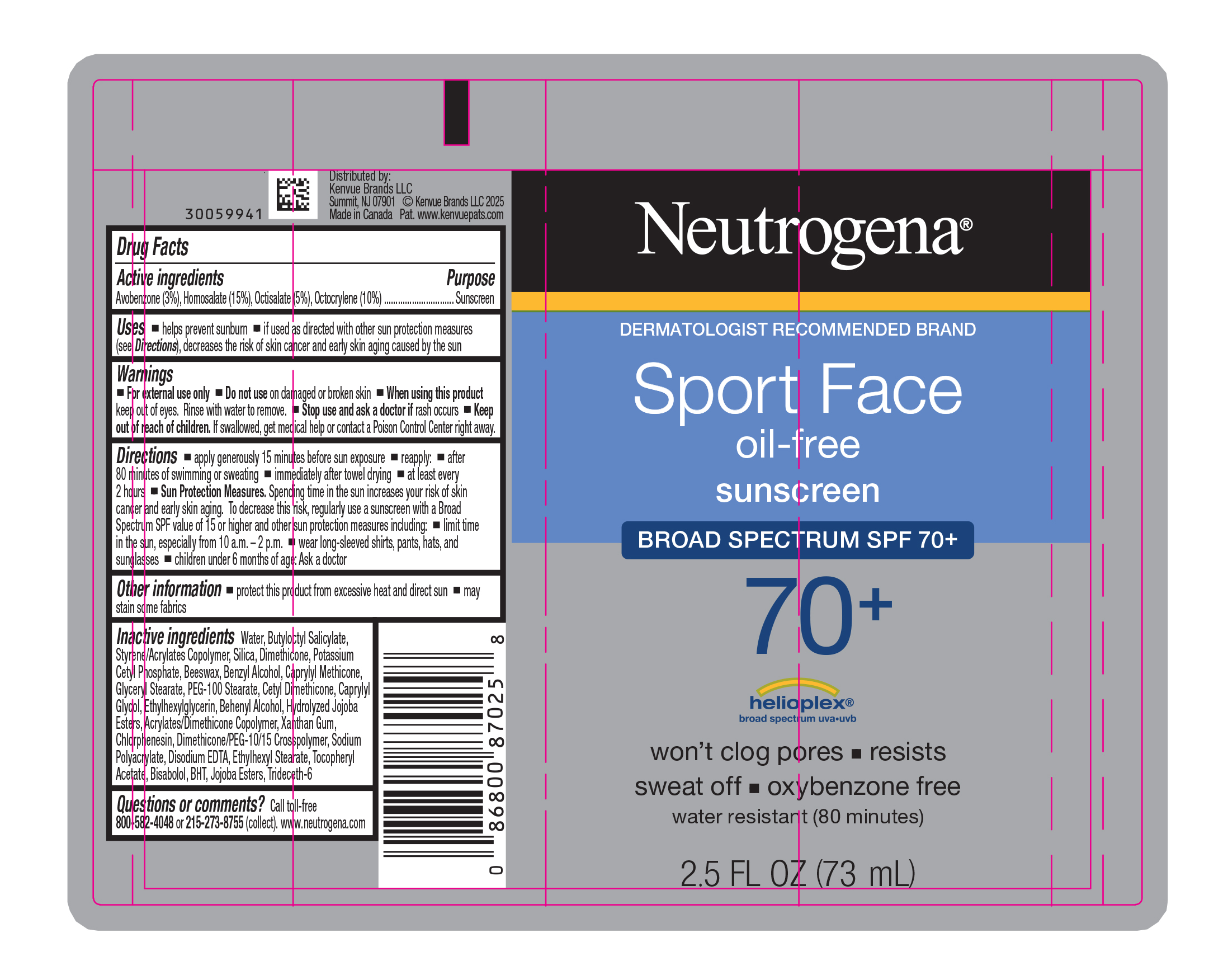 DRUG LABEL: Neutrogena Sport Face Oil Free Sunscreen Broad Spectrum SPF 70 Plus
NDC: 69968-0670 | Form: LOTION
Manufacturer: Kenvue Brands LLC
Category: otc | Type: HUMAN OTC DRUG LABEL
Date: 20250825

ACTIVE INGREDIENTS: AVOBENZONE 30 mg/1 mL; HOMOSALATE 150 mg/1 mL; OCTISALATE 50 mg/1 mL; OCTOCRYLENE 100 mg/1 mL
INACTIVE INGREDIENTS: DOCOSANOL; HYDROLYZED JOJOBA ESTERS (ACID FORM); XANTHAN GUM; CHLORPHENESIN; DIMETHICONE/PEG-10/15 CROSSPOLYMER; EDETATE DISODIUM; ETHYLHEXYL STEARATE; .ALPHA.-TOCOPHEROL ACETATE; LEVOMENOL; BUTYLATED HYDROXYTOLUENE; JOJOBA OIL, RANDOMIZED; TRIDECETH-6; WATER; BUTYLOCTYL SALICYLATE; BUTYL METHACRYLATE/METHYL METHACRYLATE/METHACRYLIC ACID/STYRENE CROSSPOLYMER; SILICON DIOXIDE; DIMETHICONE; POTASSIUM CETYL PHOSPHATE; YELLOW WAX; BENZYL ALCOHOL; CAPRYLYL TRISILOXANE; GLYCERYL MONOSTEARATE; PEG-100 STEARATE; CETYL DIMETHICONE 25; CAPRYLYL GLYCOL; ETHYLHEXYLGLYCERIN; 2-ETHYLHEXYL ACRYLATE, METHACRYLATE, METHYL METHACRYLATE, OR BUTYL METHACRYLATE/HYDROXYPROPYL DIMETHICONE COPOLYMER (30000-300000 MW)

Neutrogena® Sport Face oil-free sunscreen BRO AD SPECTRUM SPF 70+

Drug Facts

Active ingredients

Avobenzone (3%), Homosalate (15%), Octisalate (5%), Octocrylene (10%)

Purpose

Sunscreen

Uses

- helps prevent sunburn
- if used as directed with other sun protection measures (see Directions), decreases the risk of skin cancer and early skin aging caused by the sun

Warnings

- For external use only

- Do not use on damaged or broken skin

- When using this product keep out of eyes. Rinse with water to remove.

- Stop use and ask a doctor if rash occurs

- Keep out of reach of children. If swallowed, get medical help or contact a Poison Control Center right away.

Directions

- apply generously 15 minutes before sun exposure
- reapply:
  - after 80 minutes of swimming or sweating
  - immediately after towel drying
  - at least every 2 hours
- Sun Protection Measures. Spending time in the sun increases your risk of skin cancer and early skin aging. To decrease this risk, regularly use a sunscreen with a Broad Spectrum SPF value of 15 or higher and other sun protection measures including:
  - limit time in the sun, especially from 10 a.m. – 2 p.m.
  - wear long-sleeved shirts, pants, hats, and sunglasses
- children under 6 months of age: Ask a doctor

Other information

- protect this product from excessive heat and direct sun
- may stain some fabrics

Inactive ingredients

Water, Butyloctyl Salicylate, Styrene/Acrylates Copolymer, Silica, Dimethicone, Potassium Cetyl Phosphate, Beeswax, Benzyl Alcohol, Caprylyl Methicone, Glyceryl Stearate, PEG-100 Stearate, Cetyl Dimethicone, Caprylyl Glycol, Ethylhexylglycerin, Behenyl Alcohol, Hydrolyzed Jojoba Esters, Acrylates/Dimethicone Copolymer, Xanthan Gum, Chlorphenesin, Dimethicone/PEG-10/15 Crosspolymer, Sodium Polyacrylate, Disodium EDTA, Ethylhexyl Stearate, Tocopheryl Acetate, Bisabolol, BHT, Jojoba Esters, Trideceth-6

Questions or comments?

Call toll-free 800-582-4048 or 215-273-8755 (collect). www.neutrogena.com

Distributed by:
Kenvue Brands LLC
Summit, NJ 07901

PRINCIPAL DISPLAY PANEL - 73 mL Tube Label

Neutrogena®

DERMATOLOGIST RECOMMENED BRAND

Sport Face
oil-free
sunscreen

BROAD SPECTRUM SPF 70 +
70+

helioplex®
broad spectrum uva.uvb

won't clog pores ▪ resists
sweat off ▪ oxybenzone free
water resistant (80 minutes)

2.5 FL OZ (73 mL)